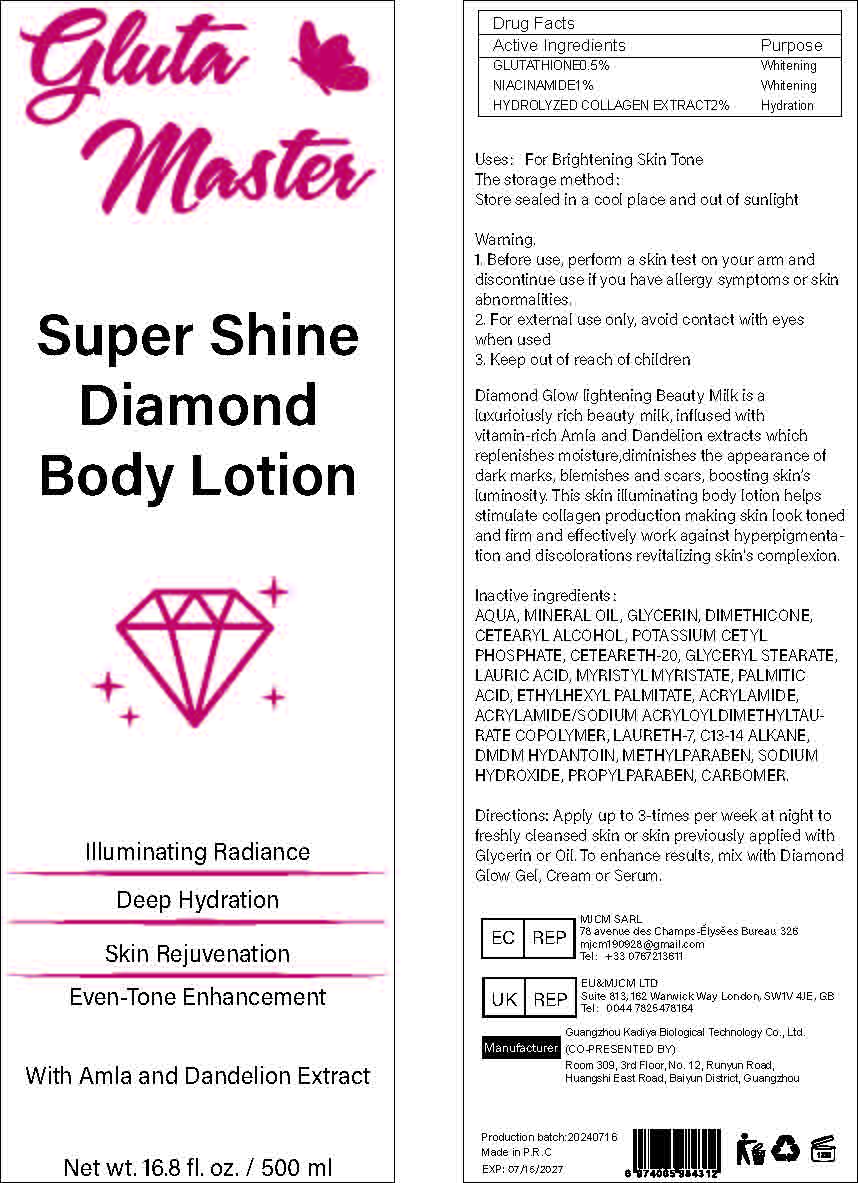 DRUG LABEL: Shine BodyLotion
NDC: 84423-028 | Form: EMULSION
Manufacturer: Guangzhou Kadiya Biotechnology Co., Ltd.
Category: otc | Type: HUMAN OTC DRUG LABEL
Date: 20240724

ACTIVE INGREDIENTS: GLUTATHIONE 5 mg/500 mL; NIACINAMIDE 2.5 mg/500 mL
INACTIVE INGREDIENTS: GLYCERIN; POTASSIUM CETYL PHOSPHATE; ACRYLAMIDE; POLYOXYL 20 CETOSTEARYL ETHER; CETOSTEARYL ALCOHOL; MINERAL OIL; PROPYLPARABEN; DIMETHICONE; MYRISTYL MYRISTATE; ETHYLHEXYL PALMITATE; DMDM HYDANTOIN; METHYLPARABEN; CARBOXYPOLYMETHYLENE; WATER; LAURETH-7; SODIUM ACRYLOYLDIMETHYLTAURATE-ACRYLAMIDE COPOLYMER (1:1; 90000-150000 MPA.S); LAURIC ACID; PALMITIC ACID; SODIUM HYDROXIDE; GLYCERYL MONOSTEARATE

Uses：
For Brightening Skin Tone

INACTIVE INGREDIENT

AQUA、MINERAL OIL、GLYCERIN、DIMETHICONE、CETEARYL ALCOHOL、POTASSIUM CETYL PHOSPHATE、CETEARETH-20、GLYCERYL STEARATE、LAURIC ACID、 MYRISTYL MYRISTATE、 PALMITIC ACID、ETHYLHEXYL PALMITATE、ACRYLAMIDE、ACRYLAMIDE/SODIUM ACRYLOYLDIMETHYLTAURATE COPOLYMER、LAURETH-7、C13-14 ALKANE、DMDM HYDANTOIN、METHYLPARABEN、SODIUM HYDROXIDE、PROPYLPARABEN、CARBOMER

Warning.
1.Before use, perform a skin test on your arm and discontinue use if you have allergy symptoms or skin abnormalities.
2、For external use only, avoid contact with eyes when used
3、Keep out of reach of children

INDICATIONS AND USAGE

Apply up to 3-times per week at night to freshly cleansed skin or skin previously applied with Glycerin or Oil.

KEEP OUT OF REACH OF CHILDREN SECTION

Active Ingredients
GLUTATHIONE 0.5%
NIACINAMIDE 1%
HYDROLYZED COLLAGEN EXTRACT 2%

DOSAGE AND ADMINISTRATION

To enhance results, mix with Diamond Glow Gel, Cream or Serum.

PACKAGE LABEL

Active Ingredients
GLUTATHIONE 0.5%
NIACINAMIDE 1%
HYDROLYZED COLLAGEN EXTRACT 2%
Uses：
For Brightening Skin Tone
The storage method：
Store sealed in a cool place and out of sunlight
Warning.
1.Before use, perform a skin test on your arm and discontinue use if you have allergy symptoms or skin abnormalities.
2、For external use only, avoid contact with eyes when used
3、Keep out of reach of children
Inactive ingredients：
AQUA、MINERAL OIL、GLYCERIN、DIMETHICONE、CETEARYL ALCOHOL、POTASSIUM CETYL PHOSPHATE、CETEARETH-20、GLYCERYL STEARATE、LAURIC ACID、 MYRISTYL MYRISTATE、 PALMITIC ACID、ETHYLHEXYL PALMITATE、ACRYLAMIDE、ACRYLAMIDE/SODIUM ACRYLOYLDIMETHYLTAURATE COPOLYMER、LAURETH-7、C13-14 ALKANE、DMDM HYDANTOIN、METHYLPARABEN、SODIUM HYDROXIDE、PROPYLPARABEN、CARBOMER